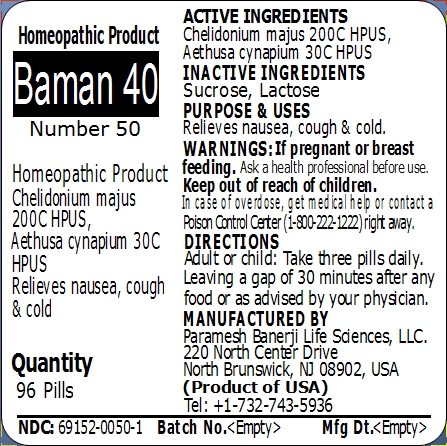 DRUG LABEL: Baman 40 (Number 50)
NDC: 69152-0050 | Form: PELLET
Manufacturer: Paramesh Banerji Life Sciences LLC
Category: homeopathic | Type: HUMAN OTC DRUG LABEL
Date: 20150223

ACTIVE INGREDIENTS: CHELIDONIUM MAJUS 200 [hp_C]/1 1; AETHUSA CYNAPIUM 30 [hp_C]/1 1
INACTIVE INGREDIENTS: SUCROSE; LACTOSE

Active Ingredients

Chelidonium majus 200C HPUS, Aethusa cynapium 30C HPUS

Inactive Ingredients

Sucrose, Lactose

Purpose

Relieves nausea, cough and cold

Uses

Relieves nausea, cough and cold

Warnings

If pregnant or breast feeding ask a health professional before use.

Keep out of reach of children. In case of overdose, get medical help or contact a Poison Control Center (1-800-222-1222) right away.

Direction

Adult or child: Take three pills daily. Leaving a gap of 30 minutes after any food or as advised by your physician.

Manufactured by

Paramesh Banerji Life Sciences, LLC

220 North Center Drive

North Brunswick, NJ 08902, USA

Product of USA

Tel: +1-732-743-5936

Principal Display Panel

Homeopathic Product

Baman 40

Number 50

Homeopathic Product

Chelidonium majus 200C HPUS, Aethusa cynapium 30C HPUS

Relieves nausea, cough and cold

Quantity

96 Pills